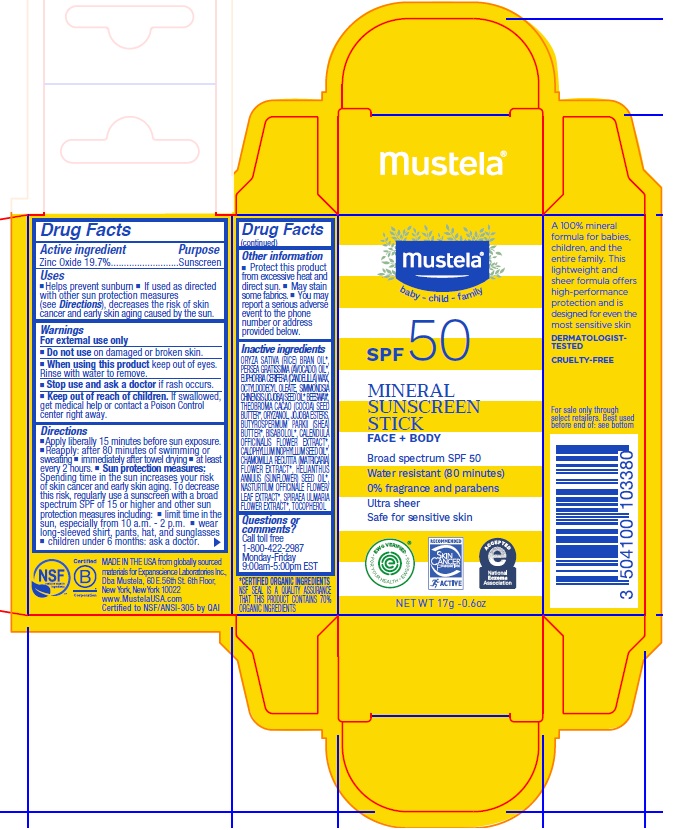 DRUG LABEL: MUSTELA MINERAL SUNSCREEN SPF 50
NDC: 64768-2926 | Form: STICK
Manufacturer: Expanscience Laboratories d/b/a Mustela
Category: otc | Type: HUMAN OTC DRUG LABEL
Date: 20241202

ACTIVE INGREDIENTS: ZINC OXIDE 197 mg/1 g
INACTIVE INGREDIENTS: CHAMOMILE; AVOCADO OIL; YELLOW WAX; ORYZANOL; COCOA BUTTER; SHEA BUTTER; LEVOMENOL; TAMANU OIL; NASTURTIUM OFFICINALE FLOWERING TOP; SUNFLOWER OIL; JOJOBA OIL; FILIPENDULA ULMARIA FLOWER; CALENDULA OFFICINALIS FLOWER; RICE BRAN OIL; OCTYLDODECYL OLEATE; JOJOBA OIL, RANDOMIZED; TOCOPHEROL; CANDELILLA WAX

MUSTELA MINERAL SUNSCREEN STICK SPF 50

Active ingredient

Zinc Oxide 19.7%

Purpose

Sunscreen

Uses

- Helps prevent sunburn
- If used as directed with other sun protection measures (see Directions), decreases the risk of skin cancer and early skin aging caused by the sun.

Warnings

For external use only

Do not use

on damaged or broken skin

When using this product

keep out of eyes. Rinse with water to remove.

Stop use and ask a doctor

if rash occurs

Keep out of reach of children.

If swallowed, get medical help or contact a Poison Control center right away.

Directions

- Apply liberally 15 minutes before sun exposure
- Reapply: after 80 minutes of swimming or sweating
- immediately after towel drying
- at least every 2 hours.
- Sun protection measures: Spending time in the sun increases your risk of skin cancer and early skin aging. To decrease this risk, regularly use a sunscreen with a broad spectrum SPF of 15 or higher and other sun protection measures including:
- limit time in the sun, especially from 10 a.m - 2p.m
- wear long-sleeved shirt, pants, hat, and sunglasses
- children under 6 months: ask a doctor.

Other information

- Protect this product from excessive heat and direct sun.
- May stain some fabrics.
- You may report a serious adverse event to the phone number or address provided below.

Inactive ingredients

ORYZA SATIVA (RICE) BRAN OIL*, PERSEA GRATISSIMA (AVOCADO) OIL*, EUPHORBIA CERIFERA (CANDELILLA) WAX, OCTYLDODECYL OLEATE, SIMMONDSIA CHINENSIS (JOJOBA) SEED OIL*, BEESWAX*, THEOBROMA CACAO (COCOA) SEED BUTTER*, ORYZANOL, JOJOBA ESTERS, BUTYROSPERMUM PARKII (SHEA) BUTTER*, BISABOLOL*, CALENDULA OFFICINALIS FLOWER EXTRACT*, CALOPHYLLUM INOPHYLLUM SEED OIL*, CHAMOMILLA RECUTITA (MATRICARIA) FLOWER EXTRACT*, HELIANTHUS ANNUUS (SUNFLOWER) SEED OIL*, NASTURTIUM OFFICINALE FLOWER/LEAF EXTRACT*, SPIRAEA ULMARIA FLOWER EXTRACT*, TOCOPHEROL

*CERTIFIED ORGANIC INGREDIENTS

Questions or comments?

Call toll free 1-800-422-2987
Monday-Friday 9:00am-5:00pm EST

Company Information

MADE IN THE USA from globally sourced materials for
Expanscience Laboratories Inc.,
Dba Mustela, 60 E. 56th St. 6th Floor, New York, New York 10022
www.MustelaUSA.com